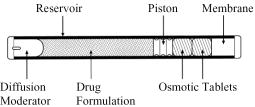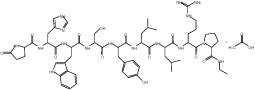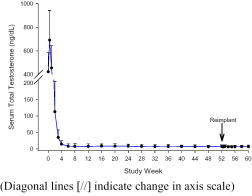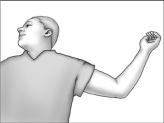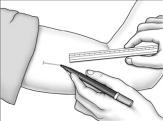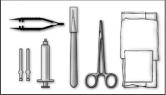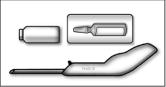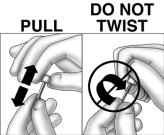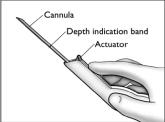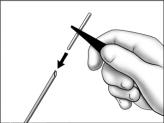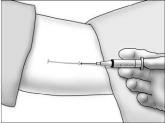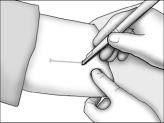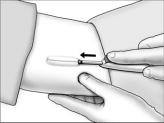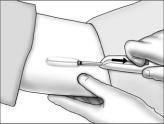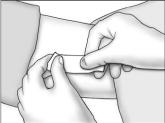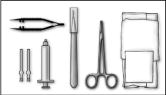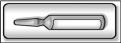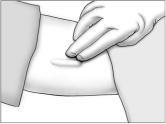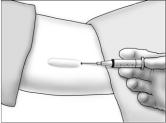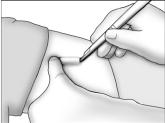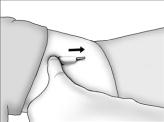 DRUG LABEL: Unknown
Manufacturer: Bayer Pharmaceuticals Corporation
Category: prescription | Type: HUMAN PRESCRIPTION DRUG LABELING
Date: 20060510

Viadur® (leuprolide acetate implant)

DESCRIPTION

Viadur® (leuprolide acetate implant) is a sterile nonbiodegradable, osmotically driven miniaturized implant designed to deliver leuprolide acetate for 12 months at a controlled rate (Figure A). Viadur® incorporates DUROS® technology. The system contains 65 mg of leuprolide (free base). Leuprolide acetate is a synthetic nonapeptide analog of naturally occurring gonadotropin-releasing hormone (GnRH or LH-RH). The analog possesses greater potency than the natural hormone. The implant is inserted subcutaneously in the inner aspect of the upper arm. After 12 months, the implant must be removed. At the time an implant is removed, another implant may be inserted to continue therapy.

Viadur® contains 72 mg of leuprolide acetate (equivalent to 65 mg leuprolide free base) dissolved in 104 mg dimethyl sulfoxide. The 4 mm by 45 mm titanium alloy reservoir houses a polyurethane rate-controlling membrane, an elastomeric piston, and a polyethylene diffusion moderator. The reservoir also contains the osmotic tablets, which are not released with the drug formulation. The osmotic tablets are composed of sodium chloride, sodium carboxymethyl cellulose, povidone, magnesium stearate, and sterile water for injection. Polyethylene glycol fills the space between the osmotic tablets and the reservoir. A minute amount of silicone medical fluid is used during manufacture as a lubricant. The weight of the implant is approximately 1.1g.

Figure A Viadur® (leuprolide acetate implant) (diagram not to scale)

The chemical name is 5-Oxo-L-prolyl-L-histidyl-L-tryptophyl-L-seryl-L-tyrosyl-D-leucyl-L-leucyl-L-arginyl-N-ethyl-L-prolinamide acetate (salt), with the following structural formula:

CLINICAL PHARMACOLOGY

Leuprolide acetate, an LH-RH agonist, acts as a potent inhibitor of gonadotropin secretion when given continuously and in therapeutic doses. Animal and human studies indicate that after an initial stimulation, chronic administration of leuprolide acetate results in suppression of ovarian and testicular steroidogenesis.

In humans, administration of leuprolide acetate results in an initial increase in circulating levels of luteinizing hormone (LH) and follicle-stimulating hormone (FSH), leading to a transient increase in concentrations of gonadal steroids (testosterone and dihydrotestosterone in males, and estrone and estradiol in premenopausal females). However, continuous administration of leuprolide acetate results in decreased levels of LH and FSH. In males, testosterone is reduced to castrate levels. These decreases occur within 2 to 4 weeks after initiation of treatment.

One Viadur® Implant nominally delivers 120 micrograms of leuprolide acetate per day over 12 months. Leuprolide acetate is not active when given orally.

PHARMACOKINETICS

Absorption

After insertion of Viadur®, mean serum leuprolide concentrations were 16.9 ng/mL at 4 hours and 2.4 ng/mL at 24 hours. Thereafter, leuprolide was released at a constant rate. Mean serum leuprolide concentrations were maintained at 0.9 ng/mL (0.3 to 3.1 ng/mL; SD = ±0.4) for 12 months. Upon removal and insertion of a new Viadur® at 12 months, steady-state serum leuprolide concentrations were maintained.

Distribution

The mean steady-state volume of distribution of leuprolide following 1 mg intravenous (IV) bolus administration to healthy male volunteers was 27 L. In vitro binding to human plasma proteins ranged from 43% to 49%.^1

Metabolism

In healthy male volunteers administered a 1 mg IV bolus of leuprolide, the mean systemic clearance was 8.34 L/h, with a terminal elimination half-life of approximately 3 hours, based on a two-compartment model.^1

A pentapeptide (M-1) is the major leuprolide metabolite upon administration with different leuprolide acetate formulations. No drug metabolism study was conducted with Viadur®.

Excretion

No drug excretion study was conducted with Viadur®.

Dose Proportionality

In a study comparing one Viadur® implant to two Viadur® implants, mean serum leuprolide concentrations were proportional to dose.

Special Populations

Geriatrics

The majority (88%) of the 131 patients studied in clinical trials were age 65 and over.

Pediatrics

The safety and effectiveness of Viadur® in pediatric patients have not been established (see CONTRAINDICATIONS).

Race

In the patients studied (80 Caucasian, 23 Black, 3 Hispanic), mean serum leuprolide concentrations were similar.

Renal and Hepatic Insufficiency

The pharmacokinetics of the drug in hepatically and renally impaired patients have not been determined.

Drug-Drug Interactions

No pharmacokinetic drug-drug interaction studies were conducted with Viadur®.

CLINICAL STUDIES

In two open-label, non-comparative, multicenter studies, 131 patients with prostatic cancer were treated with Viadur® and evaluated for up to two years. Two-thirds of the patients had stage C or less advanced disease. The dose-ranging study assessed serum testosterone as the primary efficacy endpoint in 51 patients treated with either one [n=27] or two [n=24] implants for 12 months. The confirmatory study evaluated achievement and maintenance of serum testosterone suppression in 80 patients each treated with one implant for 12 months. Both studies included a removal procedure and insertion of a new implant with evaluation for 12 additional months.

Following the initial insertion in patients receiving one implant, mean serum testosterone concentrations increased from 422 ng/dL at baseline to 690 ng/dL on Day 3, then decreased to below baseline by week two (Figure B). Serum testosterone decreased below the 50 ng/dL castrate threshold by week four in all but one patient [106 of 107 patients, 99%]. Once serum testosterone suppression was achieved [one patient was not continuously suppressed until week 28], testosterone remained suppressed below the castrate threshold for the duration of the treatment phase.

Figure B Mean (+SD) Serum Total Testosterone Concentrations – All Patients (n=107) Who Received One Implant

Most patients [n=118] had a new implant inserted for a second year of therapy following removal of the first implant(s). No patient experienced a clinically significant increase in serum testosterone [acute-on-chronic phenomenon] upon removal of the original implant(s) and insertion of a new implant. Suppression of serum testosterone was maintained in all patients through the two-month follow-up period following removal of the first implant(s) and insertion of a new implant.

Serum Prostate Specific Antigen (PSA) was monitored as a secondary endpoint in the clinical studies with Viadur®. Serum PSA decreased in all patients after they began treatment with Viadur®. At six months, PSA concentrations decreased from baseline by at least 90% in 74.2% of the 97 evaluable patients.

Periodic monitoring of serum testosterone and PSA concentrations is recommended, especially if the anticipated clinical or biochemical response to treatment has not been achieved.

INDICATIONS AND USAGE

Viadur® is indicated in the palliative treatment of advanced prostate cancer.

CONTRAINDICATIONS

1. Viadur® is contraindicated in patients with hypersensitivity to GnRH, GnRH agonist analogs, or any of the components in Viadur®. Anaphylactic reactions to synthetic GnRH or GnRH agonist analogs have been reported in the literature.^2
2. Viadur® is contraindicated in women and in pediatric patients and was not studied in women or children. Moreover, leuprolide acetate can cause fetal harm when administered to a pregnant woman. Major fetal abnormalities were observed in rabbits but not in rats after administration of leuprolide acetate throughout gestation. There were increased fetal mortality and decreased fetal weights in rats and rabbits. The effects on fetal mortality are expected consequences of the alterations in hormonal levels brought about by this drug. The possibility exists that spontaneous abortion may occur.

WARNINGS

Viadur®, like other LH-RH agonists, causes a transient increase in serum concentrations of testosterone during the first week of treatment. Patients may experience worsening of symptoms or onset of new symptoms, including bone pain, neuropathy, hematuria, or ureteral or bladder outlet obstruction (see PRECAUTIONS).

Cases of ureteral obstruction and spinal cord compression, which may contribute to paralysis with or without fatal complications, have been reported with LH-RH agonists.

If spinal cord compression or renal impairment develops, standard treatment of these complications should be instituted.

PRECAUTIONS

General

Patients with metastatic vertebral lesions and/or with urinary tract obstruction should be closely observed during the first few weeks of therapy (see WARNINGS).

X-rays do not affect Viadur® functionality. Viadur® is radio-opaque and is well visualized on X-rays.

The titanium alloy reservoir of Viadur® is nonferromagnetic and is not affected by magnetic resonance imaging (MRI). Slight image distortion around Viadur® may occur during MRI procedures.

Information for Patients

An information leaflet for patients is included with the product.

Laboratory tests

Response to Viadur® should be monitored by measuring serum concentrations of testosterone and prostate-specific antigen periodically.

Results of testosterone determinations are dependent on assay methodology. It is advisable to be aware of the type and precision of the assay methodology to make appropriate clinical and therapeutic decisions.

Drug Interactions

See PHARMACOKINETICS.

Drug/Laboratory Test Interactions

Therapy with leuprolide results in suppression of the pituitary-gonadal system. Results of diagnostic tests of pituitary gonadotropic and gonadal functions conducted during and after leuprolide therapy may be affected.

Carcinogenesis, Mutagenesis, Impairment of Fertility

Two-year carcinogenicity studies were conducted in rats and mice. In rats, dose-related increases of benign pituitary hyperplasia and benign pituitary adenomas were noted at 24 months when the drug was administered subcutaneously at high daily doses (4 to 24 mg/m^2, 50 to 300 times the daily human exposure based on body surface area). There were significant but not dose-related increases of pancreatic islet-cell adenomas in females and of testicular interstitial cell adenomas in males (highest incidence in the low dose group). In mice no pituitary abnormalities were observed at up to 180 mg/m^2 (over 2000 times the daily human exposure based on body surface area) for 2 years.

Mutagenicity studies were performed with leuprolide acetate using bacterial and mammalian systems. These studies provided no evidence of a mutagenic potential.

Pregnancy, Teratogenic Effects

Pregnancy Category X (see CONTRAINDICATIONS).

Pediatric Use

Viadur® is contraindicated in pediatric patients and was not studied in children

(see CONTRAINDICATIONS).

ADVERSE REACTIONS

The safety of Viadur® was evaluated in 131 patients with prostate cancer treated for up to 24 months in two clinical trials. Viadur®, like other LHRH analogs, caused a transient increase in serum testosterone concentrations during the first 2 weeks of treatment. Therefore, potential exacerbations of signs and symptoms of the disease during the first few weeks of treatment are of concern in patients with vertebral metastases and/or urinary obstruction or hematuria. If these conditions are aggravated, it may lead to neurological problems such as weakness and/or paresthesia of the lower limbs or worsening of urinary symptoms (see WARNINGS and PRECAUTIONS).

In the above-described clinical trials, the transient increase in serum testosterone concentrations was associated with an exacerbation of disease symptoms, manifested by pain or bladder outlet obstructive symptoms (urinary retention or frequency) in 6 (4.6%) patients.

The majority of local reactions associated with initial insertion or removal and insertion of a new implant began and resolved within the first two weeks. Reactions persisted in 9.3% of patients. 10.3% of patients developed application-site reactions after the first two weeks following insertion.

Local reactions after initial insertion of a single implant included bruising (34.6%) and burning (5.6%). Other, less frequently reported, reactions included pulling, pressure, itching, erythema, pain, edema, and bleeding.

In these two clinical trials, four patients had local infection/inflammations that resolved after treatment with oral antibiotics.

Local reactions following insertion of a subsequent implant were comparable to those seen after initial insertion.

In the first 12 months after initial insertion of the implant(s), an implant extruded through the incision site in three of 131 patients (see INSERTION AND REMOVAL PROCEDURES for correct implant placement).

The following possibly or probably related systemic adverse events occurred during clinical trials within 24 months of treatment with Viadur®, and were reported in ≥2% of patients (Table 1).

Table 1 Incidence (%) of Possibly or Probably Related Systemic Adverse Events Reported by ≥ 2% of Patients Treated with Viadur® for up to 24 Months
Body System | Adverse Event | Number (%)
Body as a Whole | Asthenia | 10 (7.6%)
 | Headache | 6 (4.6%)
 | Extremity pain | 4 (3.1%)
Cardiovascular | Vasodilatation (hot flashes)* | 89 (67.9%)
Digestive | Diarrhea | 3 (2.3%)
Hematology and Lymphatic | Ecchymosis | 6 (4.6%)
 | Anemia | 3 (2.3%)
Metabolic and Nutritional | Peripheral edema | 4 (3.1%)
 | Weight gain | 3 (2.3%)
Nervous | Depression | 7 (5.3%)
Respiratory | Dyspnea | 3 (2.3%)
Skin | Sweating* | 7 (5.3%)
 | Alopecia | 3 (2.3%)
Urogenital | Gynecomastia/breast enlargement* | 9 (6.9%)
 | Nocturia | 5 (3.8%)
 | Urinary frequency | 5 (3.8%)
 | Testis atrophy or pain* | 5 (3.8%)
 | Breast pain* | 4 (3.1%)
 | Impotence* | 3 (2.3%)
* Expected pharmacologic consequences of testosterone suppression.

In addition, the following possibly or probably related systemic adverse events were reported by <2% of patients using Viadur® in clinical studies.

General: General pain, chills, abdominal pain, malaise, dry mucous membranes

Gastrointestinal: Constipation, nausea

Hematologic: Iron deficiency anemia

Metabolic: Edema, weight loss

Musculoskeletal: Bone pain, arthritis

Nervous: Dizziness, insomnia, paresthesia, amnesia, anxiety

Skin: Pruritus, rash, hirsutism

Urogenital: Urinary urgency, prostatic disorder, urinary tract infection, dysuria, urinary incontinence, urinary retention

Changes in Bone Density

Decreased bone density has been reported in the medical literature in men who have had orchiectomy or who have been treated with an LH-RH agonist analog. In a clinical trial, 25 men with prostate cancer, 12 of whom had been treated previously with leuprolide acetate for at least 6 months, underwent bone density studies as a result of pain. The leuprolide-treated group had lower bone density scores than the nontreated control group. It can be anticipated that long periods of medical castration in men will have effects on bone density.

Postmarketing

Pituitary apoplexy: During post-marketing surveillance, rare cases of pituitary apoplexy (a clinical syndrome secondary to infarction of the pituitary gland) have been reported after the administration of gonadotropin-releasing hormone agonists. In a majority of these cases, a pituitary adenoma was diagnosed with a majority of pituitary apoplexy cases occurring within 2 weeks of the first dose, and some within the first hour. In these cases, pituitary apoplexy has presented as sudden headache, vomiting, visual changes, ophthalmoplegia, altered mental status, and sometimes cardiovascular collapse. Immediate medical attention has been required.

Ninety-seven of the 131 patients in the two-year duration studies that supported approval of Viadur® continued in an open-label, third-year extension study. One patient prematurely withdrew due to lack of efficacy that was attributed to a defective implant. Fifty of these patients continued in an open-label, fourth-year extension study. No spontaneous implant extrusions were reported in these extension studies. Since Viadur® has been commercially available, <1% of patients implanted have been reported to have a spontaneous implant extrusion (with or without associated infection).

Additional adverse events have been reported from US post-marketing experience with Viadur®. Because these events are reported voluntarily from a population of uncertain size, it is not always possible to reliably estimate their frequency or establish a causal relationship to drug exposure. These events have been reported infrequently and include fatigue, hypertension, migration of implant, syncope, tremor, and vomiting.

OVERDOSAGE

In clinical trials using daily subcutaneous leuprolide acetate in patients with prostate cancer, doses as high as 20 mg/day for up to 2 years caused no adverse effects differing from those observed with the 1 mg/day dose. The adverse event profiles were similar in patients receiving one or two Viadur® implants.

DOSAGE AND ADMINISTRATION

The recommended dose of Viadur® is one implant for 12 months. Each implant contains 65 mg leuprolide. The implant is inserted subcutaneously in the inner aspect of the upper arm and provides continuous release of leuprolide for 12 months of hormonal therapy.

Viadur® must be removed after 12 months of therapy. At the time an implant is removed, another implant may be inserted to continue therapy. (See INSERTION AND REMOVAL PROCEDURES.)

Insertion and Removal Procedures

Viadur® is supplied in a box containing one sterile Viadur® implant in a sealed vial, one Viadur® sterile implanter, one sealed container of lidocaine HCl USP 2%, 10 mL, and one sterile Viadur® Kit. The Viadur® Kit is designed to provide a sterile field and supplies to facilitate the insertion and/or subsequent removal of the implant.

In addition to the Viadur® Kit, sterile gloves are required for the insertion procedure and subsequent removal of the implant.

Insertion Procedure

Under aseptic conditions, an implanter is used to place the implant under the skin.

The implant is inserted using the procedure outlined below.

Identifying the Insertion Site

1. Have the patient lie on his back on the examination table, with his left arm (if the patient is left-handed, the right arm) flexed at the elbow and externally rotated so that his hand is out to his side.
  Using a pen and ruler, mark a site on the inner, upper arm approximately 8-10 cm above the elbow crease in the groove between the biceps and triceps muscles. Make sure that the site is unaffected by movement of the muscles.

Preparing the Sterile Field

1. To establish a sterile field, carefully open the sterile Viadur® Kit. The sterile kit contains:
  1 scalpel
  1 forceps
  1 syringe
  1 package povidone-iodine swabs
  1 package wound closure strips
  1-22 Ga x 1.5” needle
  1-25 Ga x 1.5” needle
  6 gauze sponges
  2 alcohol prep swabs
  1 package skin protectant
  1 bandage
  1 fenestrated drape
  1 marking pen
  1 ruler
  1 mosquito clamp
2. The implant tray contains:
  1 sealed vial, which contains the Viadur® implant
  1 sterile implanter
  1 sealed container of lidocaine HCl USP 2%, 10 mL

To open the vial, remove the metal band from the bottle and pull up the stopper. Carefully drop the implant from the bottle onto the sterile field. Then, carefully drop the implanter and the container of lidocaine onto the sterile field.

Using sterile technique, remove the protective cap from the implant by pulling the cap straight off. DO NOT TWIST CAP OFF AS IT MAY UNSCREW THE DIFFUSION MODERATOR, CAUSE ITS REMOVAL, OR OTHERWISE DAMAGE THE IMPLANT. SHOULD DAMAGE OCCUR, DO NOT INSERT THE IMPLANT AS PRODUCT FUNCTION CAN BE IMPAIRED.

Loading the Implanter

1. The implanter is packaged in the correct configuration for implant loading and insertion. Make sure the cannula is fully extended as shown, and the actuator is in its most forward position.
2. Using sterile forceps, slide the implant into the end of the cannula and push until it stops. When properly loaded, the implant should not protrude more than 1 mm past the bottom of the beveled edge.

Inserting the Implant

1. Using aseptic technique, cleanse the insertion site, then drape the patient's arm. After determining the absence of known allergies to the anesthetic agent, infiltrate the site with lidocaine. Advance the needle to infiltrate the intended 5 cm track for the implant insertion.
2. Determine that anesthesia is adequate. Make an incision of approximately 5 mm with the scalpel, just through the dermis.
3. Grasp the handle of the implanter and extend the index finger to rest on the back of the actuator as shown. Insert the cannula tip into the incision with the bevel up and advance it subcutaneously along the intended track. To ensure subcutaneous placement, the Viadur® implanter should visibly raise the skin at all times during insertion. The implanter should not enter muscle tissue, but be well within the subcutaneous space. Advance the implanter to the depth indicator on the cannula, which indicates the recommended insertion length.
4. Holding the implanter handle in position, use the index finger to slide the actuator slowly back until it stops. (This retracts the actuator cannula into the handle, leaving the implant beneath the skin.). Do not pull back on the implanter handle while sliding the actuator back, as this may lead to incorrect positioning of the implant and subsequent extrusion. Withdraw the implanter from the incision. Release of the implant can be checked by palpation. It is important to keep the implanter steady and not to push the implant into the tissue. After placement, sterile gauze may be used to apply pressure briefly to the insertion site to ensure hemostasis.
5. Cleanse the insertion area. Press the edges of the incision together, and tightly close the incision with one or two surgical closure strips. Cover with an adhesive bandage. Observe the patient for a few minutes for signs of bleeding from the incision before he is discharged. Instruct the patient to keep the area clean and dry for 24 hours, and to avoid heavy lifting and strenuous physical activity for 48 hours. The surgical closure strip can be removed as soon as the incision has healed, ie, normally in 3 days.

Removal Procedure

Viadur® must be removed following 12 months of therapy.

The position of the patient and the sterile technique are the same as for insertion.

To remove Viadur® use the Viadur® Kit or the following sterile items:

1 scalpel
1 forceps
1 syringe
1 package povidone-iodine swabs
1 package wound closure strips
1-22 Ga x 1.5” needle
1-25 Ga x 1.5” needle
1 sealed container of lidocaine HCl USP 2%, 10 mL
6 gauze sponges
2 alcohol prep swabs
1 package skin protectant
1 bandage
1 fenestrated drape
1 marking pen
1 ruler
1 mosquito clamp

Preparing the Site

1. Inspect the site, palpating the location of the implant. Mark the position of the implant with marking pen. Cleanse with povidone-iodine swab. Drape the area with a fenestrated drape.
  Suggestion:
  If unable to locate by palpation, radiological imaging may be helpful.
2. After determining the absence of known allergies to the anesthetic agent, apply a small amount of local anesthetic under the end of the implant nearest the original incision site. Then advance the needle to infiltrate the tissue along the track.

Removing the Implant

1. Determine that anesthesia is adequate. Apply pressure to one end of the implant to elevate the other end. Make an incision of approximately 5 mm at the elevated end of the implant. Do not make a large incision.
  Continue to apply pressure to the end of the implant to encourage expulsion. Push the implant gently towards the incision with the fingers. When the tip is visible or near the incision, grasp it with a clamp and remove.
2. If necessary, cut through any fibrous encapsulation with the scalpel to free the implant.
3. Properly dispose of removed implant immediately, before opening the vial containing the new implant.
  If inserting a new Viadur®, return to section describing INSERTION PROCEDURE.
  The new Viadur® implant may be placed through the same incision site. Alternatively, the contralateral arm may be used.
4. Cleanse insertion site area. Apply pressure to each end of the incision to close the wound. Apply one or two surgical closure strips to close the wound tightly, and cover with an adhesive bandage. Observe the patient for a few minutes for signs of bleeding from the incision before he is discharged. Instruct the patient to keep the area clean and dry for 24 hours, and to avoid strenuous physical activity for 48 hours.

HOW SUPPLIED

Viadur® is supplied in a box containing 2 inner package trays. One tray contains a sterile Viadur® implant in a sealed vial, a sterile Viadur® implanter and a sealed container of lidocaine HCl USP 2%, 10 mL. The other tray constitutes a sterile Viadur® Kit, which includes: 1 scalpel, 1 forceps, 1 syringe, povidone-iodine swabs, 1 package wound closure strips, 1-22 Ga x 1.5” needle, 1-25 Ga x 1.5” needle, 6 gauze sponges, 2 alcohol prep swabs, 1 package skin protectant, 1 bandage, 1 fenestrated drape, 1 marking pen, 1 ruler, and 1 mosquito clamp. A physician insert, patient information, and insertion and removal instructions are also provided in the box.

(NDC 0026-9711-01)

Rx Only

Store at 25°C (77°F); excursions permitted to 15-30°C (59-86°F). [see USP Controlled Room Temperature]

For more information call 1-800-288-8371 or visit www.VIADUR.com.

REFERENCES

1. Sennello LT et al. Single-dose pharmacokinetics of leuprolide in humans following intravenous and subcutaneous administration. J Pharm Sci 1986; 75(2): 158-160.
2. MacLeod TL et al. Anaphylactic reaction to synthetic luteinizing hormone-releasing hormone. Fertil Steril 1987; 48(3): 500-502.

Manufactured by:
ALZA Corporation
Mountain View, CA 94043 U.S.A.

Distributed by:
Bayer Pharmaceuticals Corporation
400 Morgan Lane, West Haven, CT 06516 USA

Viadur® and DUROS® are registered trademarks of ALZA Corporation under license to Bayer Pharmaceuticals Corporation. For further information about the product contact Bayer Pharmaceuticals Corporation.

An ALZA DUROS® Technology Product

Edition Date: November 2005

SUPPLEMENTAL PATIENT MATERIAL

PATIENT INFORMATION ABOUT:

Viadur®(leuprolide acetate implant)

Important Information for Patients Using Viadur® for the treatment of symptoms of advanced prostate cancer.

Please read this information before you start using Viadur®. Each time another Viadur® is inserted, check the patient information leaflet for any new information. Remember, this information does not take the place of your doctor's instructions. Ask your doctor or pharmacist if you have questions or want more information about Viadur®.

What is Viadur®?

Viadur® is a drug-delivery system that contains the drug leuprolide and is placed under the skin. It looks like a small, thin metal tube. After it is placed under the skin, Viadur® delivers leuprolide to your body continuously for 12 months.

How does Viadur®work?

Leuprolide, the active medication in Viadur®, works by reducing the testosterone produced by the testicles. This lowers the amount of testosterone in the body. Testosterone appears to be needed by prostate cancer cells. Usually prostate cancer shrinks or stops growing when the body's supply of testosterone is lowered.

By lowering the amount of testosterone in the body, Viadur® may help relieve the pain, urinary problems, and other symptoms of prostate cancer. However, Viadur® is not a cure for prostate cancer. Once Viadur® is removed by your doctor, your body will start producing testosterone again.

How is Viadur®given?

Viadur® will be placed under the skin of your upper, inner arm. The doctor will numb your arm, make a small incision, and then place Viadur® under the skin. The incision will be closed with special surgical tape and covered with a bandage. You should keep the bandage in place for a few days until the incision heals.

After 12 months, Viadur® must be removed and may be replaced with a new Viadur® by your doctor.

What should I avoid while Viadur®is inserted?

After Viadur® is inserted, keep the site clean and dry for 24 hours. Do not bathe or swim for 24 hours. Avoid heavy lifting and physical activity for 48 hours. Avoid bumping the site for a few days. After the cut has healed, you should be able to go back to your normal activities.

What should I know about using Viadur®?

- If you notice unusual bleeding, redness or pain at the insertion site, contact your doctor.
- In the first few weeks of treatment, if you experience increased pain throughout your body, weakness, or numbness, contact your doctor.
- X-rays and MRI do not affect Viadur®.
- Viadur® is seen on X-rays. Slight image distortion around Viadur® may occur during MRI procedures.
- Viadur® must be removed and may be replaced after 12 months.

Who should NOT use Viadur®?

Do not use Viadur® if you are allergic to the drug leuprolide.

Do not use Viadur® if you are a woman. Viadur® is not approved for use by women of any age. Furthermore, use of Viadur® in a woman who is or may become pregnant may cause harm to the baby. You may lose your baby through a miscarriage if the drug is used while you are pregnant.

Viadur® was not studied in children and should not be used in children.

What are the most common side effects of Viadur®?

The most common side effects related to Viadur® were hot flashes, lack of energy, depression, sweating, headache, bruising, and breast enlargement.

Prostate cancer-related symptoms may become worse during the first few weeks of treatment.

Like other similar treatment options, Viadur® may cause impotence.

There may be some pain and discomfort during and after Viadur® insertion and removal. Bruising may occur. Reactions, such as itching and redness, are usually mild and heal without treatment within two weeks. If they do not heal, contact your doctor.

There is a chance that your bones may become thinner if you use this type of drug for long periods of time. Ask your doctor if this is a risk for you.

This list is not a complete list of all the possible side effects. If you need more information, or are worried about these or other side effects, talk to your doctor or pharmacists.

What tests will my doctor perform during my treatment with Viadur®?

Your doctor may measure blood levels of testosterone and prostate-specific antigen (PSA) during your treatment with Viadur®.

Can I take Viadur®with other medications?

Tell your doctor or pharmacist about any medicines that you are taking, including Viadur®, prescription, non-prescription, and herbal remedies. Do not start taking a new medicine before checking with your doctor or pharmacist.

For more information on Viadur®, talk to your doctor or pharmacist, call 1-800-288-8371 between 8:30 AM and 5 PM Eastern Standard Time, or visit www.VIADUR.com on the Internet.